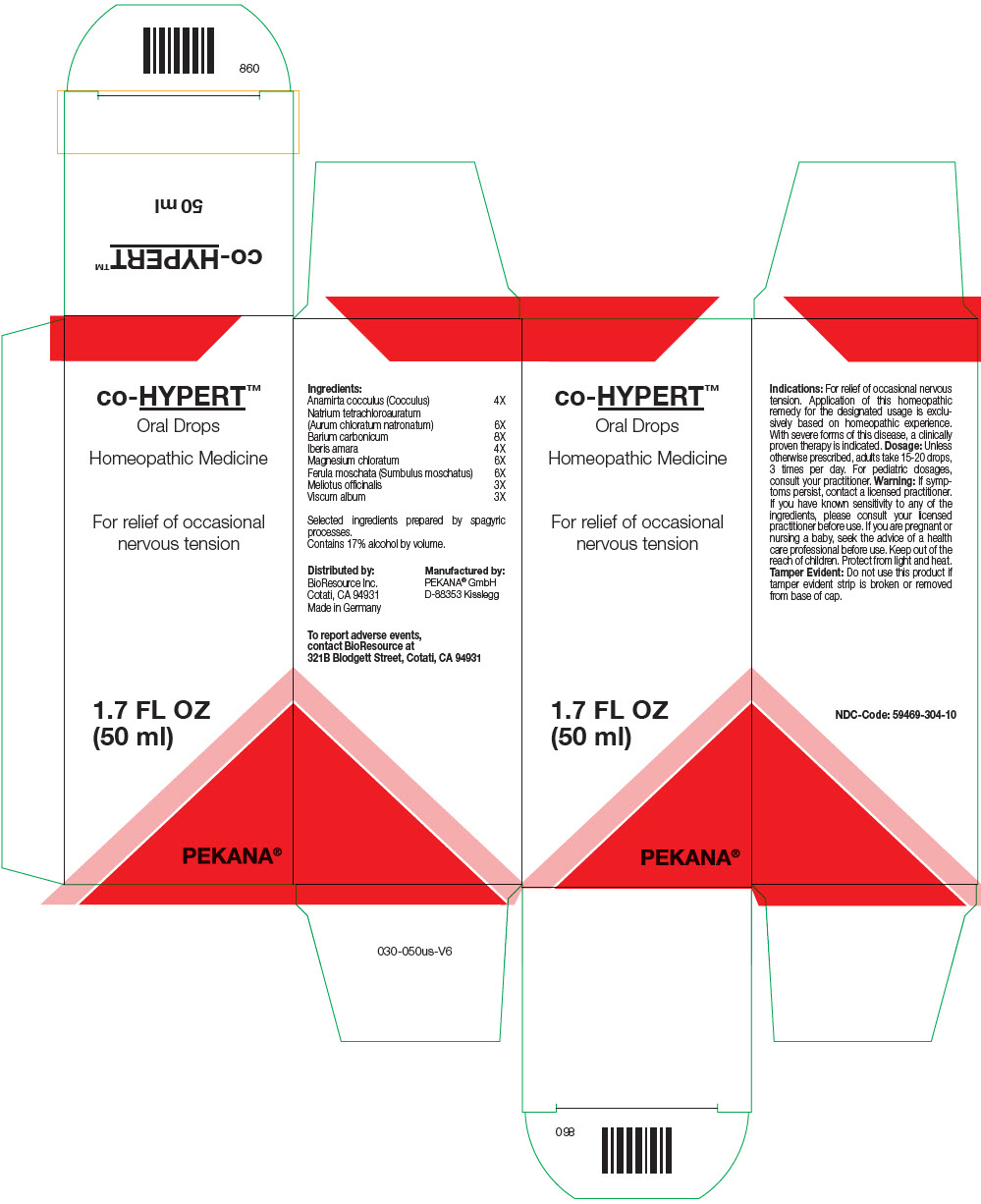 DRUG LABEL: co-HYPERT
NDC: 59469-304 | Form: SOLUTION/ DROPS
Manufacturer: PEKANA Naturheilmittel Gmbh
Category: homeopathic | Type: HUMAN OTC DRUG LABEL
Date: 20230111

ACTIVE INGREDIENTS: SODIUM TETRACHLOROAURATE 6 [hp_X]/50 mL; BARIUM CARBONATE 8 [hp_X]/50 mL; ANAMIRTA COCCULUS SEED 4 [hp_X]/50 mL; IBERIS AMARA SEED 4 [hp_X]/50 mL; MAGNESIUM CHLORIDE 6 [hp_X]/50 mL; FERULA SUMBUL ROOT 6 [hp_X]/50 mL; MELILOTUS OFFICINALIS TOP 3 [hp_X]/50 mL; VISCUM ALBUM FRUITING TOP 3 [hp_X]/50 mL
INACTIVE INGREDIENTS: WATER; ALCOHOL

co-HYPERT™

ACTIVE INGREDIENT

Ingredients:
Anamirta cocculus (Cocculus) | 4X
Natrium tetrachloroauratum (Aurum chloratum natronatum) | 6X
Barium carbonicum | 8X
Iberis amara | 4X
Magnesium chloratum | 6X
Ferula moschata (Sumbulus moschatus) | 6X
Meliotus officinalis | 3X
Viscum album | 3X

Selected ingredients prepared by spagyric processes.

INACTIVE INGREDIENT

Contains 17% alcohol by volume.

Indications

PURPOSE

For relief of occasional nervous tension. Application of this homeopathic remedy for the designated usage is exclusively based on homeopathic experience. With severe forms of this disease, a clinically proven therapy is indicated.

Dosage

Unless otherwise prescribed, adults take 15-20 drops, 3 times per day. For pediatric dosages, consult your practitioner.

Warning

ASK DOCTOR

If symptoms persist, contact a licensed practitioner. If you have known sensitivity to any of the ingredients, please consult your licensed practitioner before use. If you are pregnant or nursing a baby, seek the advice of a health care professional before use.

Keep out of the reach of children.

STORAGE AND HANDLING

Protect from light and heat.

Tamper Evident

Do not use this product if tamper evident strip is broken or removed from base of cap.

QUESTIONS

To report adverse events, contact BioResource at 321B Blodgett Street, Cotati, CA 94931

Distributed by:
BioResource Inc.
Cotati, CA 94931

Manufactured by:
PEKANA® GmbH
D-88353 Kisslegg

PRINCIPAL DISPLAY PANEL - 50 ml Bottle Box

co-HYPERT™

Oral Drops

Homeopathic Medicine

For relief of occasional
nervous tension

1.7 FL OZ
(50 ml)

PEKANA®